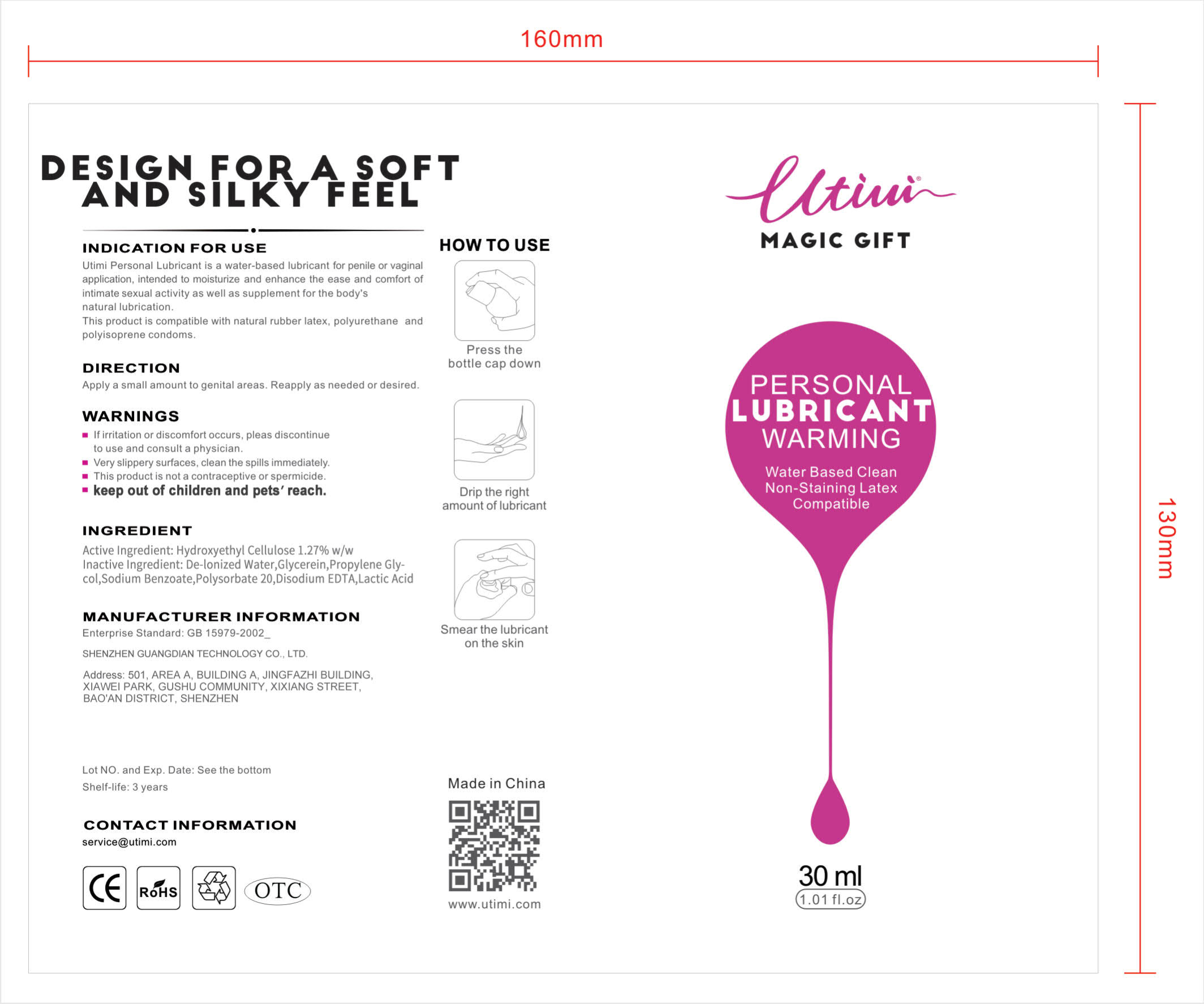 DRUG LABEL: UTIMI water based personal lubricant
NDC: 82624-101 | Form: LOTION
Manufacturer: Shenzhen Guangdian Technology Co., Ltd
Category: homeopathic | Type: HUMAN OTC DRUG LABEL
Date: 20220319

ACTIVE INGREDIENTS: HYDROXYETHYL CELLULOSE (140 CPS AT 5%) 393 mg/30 mL
INACTIVE INGREDIENTS: SODIUM BENZOATE; WATER; POLYSORBATE 20; GLYCERIN; PROPYLENE GLYCOL; LACTIC ACID, DL-; EDETATE DISODIUM ANHYDROUS

Water Based Personal Lubricant, UTIMI, 30mL

Active ingredient

Hydroxyethyl Cellulose 1.27% w/w

Inactive ingredient

De-lonized Water, Glycerin, Propylene Glycol, Sodium Benzoate, Polysorbate 20, Disodium EDTA, Lactic Acid

Indication for use

Utimi Personal Lubricant is a water-based lubricant for penile or vaginal application, intended to moisturize and enhance the ease and comfort of intimate sexual activity as well as supplement for the body's natural lubrication.

This product is compatible with natural rubber latex, polyurethane and polyisoprene condoms.

Do not use

This product is not a contraceptive or spermicide.

Stop use

If irriation or discomfor occurs, please discontinue to use and consult a physician.

Very slippery surfaces, clean the spills immediately.

Ask doctor/physician

If irriation or discomfor occurs, please discontinue to use and consult a doctor/physician.

Keep out of reach of children

Keep out of children and pets' reach.

Questions

Please contact us when you have any questions at service@utimi.com

Indications & usage

Utimi Personal Lubricant is a water-based lubricant for penile or vaginal application, intended to moisturize and enhance the ease and comfort of intimate sexual activity as well as supplement for the body's natural lubrication.

This product is compatible with natural rubber latex, polyurethane and polyisoprene condoms.

This product is not a contraceptive or spermicide.

Direction

Apply a small amount to genital areas. Reapply as needed or desired.

Dosage forms & strengths

The lubricant is like oil form.

The active ingredient strength is 1.27% w/w.

Warnings

- If irriation or discomfort occurs, please discontinue to use and consult a physician.
- Very slippery surfaces, clean the spills immediately.
- This product is not a contraceptive or spermicide.
- Keep out of children and pets' reach.